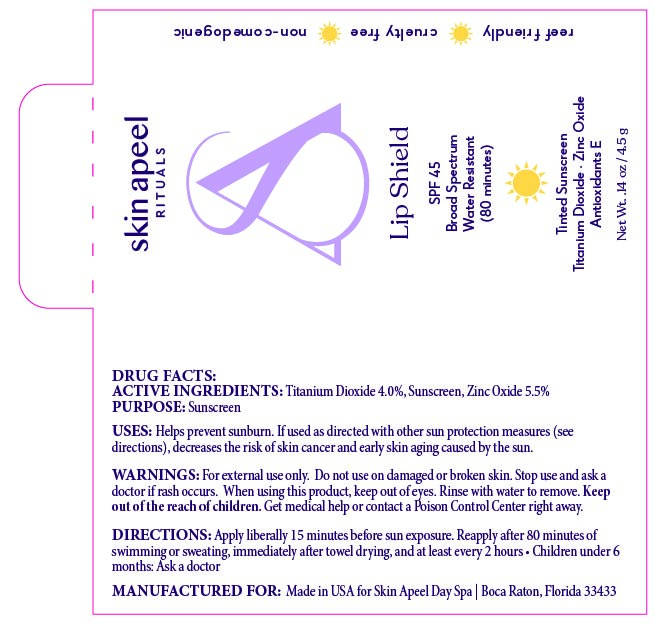 DRUG LABEL: Lip Shield
NDC: 83628-212 | Form: STICK
Manufacturer: Skin Apeel, Inc.
Category: otc | Type: HUMAN OTC DRUG LABEL
Date: 20251208

ACTIVE INGREDIENTS: TITANIUM DIOXIDE 40 mg/1 g; ZINC OXIDE 55 mg/1 g
INACTIVE INGREDIENTS: CETEARYL ISONONANOATE; DIPROPYLENE GLYCOL CAPRATE/CAPRYLATE DIESTER; CI 77492; PEG/PPG-15/15 DIMETHICONE; CERESIN; ASCORBIC ACID; POLYHYDROXYSTEARIC ACID (2300 MW); ALUMINUM STEARATE; ASCORBYL PALMITATE; ETHYLHEXYL PALMITATE; POLYGLYCERYL-3 DIISOSTEARATE; STEARIC ACID; ZINGIBER OFFICINALE (GINGER) ROOT OIL; LECITHIN, SOYBEAN; CI 77491; HEXYLDECANOL; TOCOPHEROL; ALPHA-TOCOPHEROL ACETATE; ALUMINUM HYDROXIDE; HEXYLDECYL LAURATE; CETYL DIMETHYLBUTYL ETHER; C12-15 ALKYL BENZOATE; PEG-8; HELIANTHUS ANNUUS (SUNFLOWER) SEED WAX; CI 77499; ALUMINA; CITRIC ACID

Active Ingredients:

Titanium Dioxide: 4%

Zinc Oxide: 5.5%

Purpose:

Sunscreen

Uses:

Helps Prevent Sunburn. If used as directed with other sun protection measures (see “Directions”), decreases the risk of skin cancer and early skin aging caused by the sun.

Warnings:

For external use only. Do not use on broken or damaged skin. Stop use and ask a doctor if rash occurs. When using this product, keep out of eyes. Rinse with water to remove. Keep out of reach of children. If swallowed, get medical help or contact a poison control center right away.

Warnings:

Keep out of reach of children

Directions:

Apply liberally 15 minutes before sun exposure. Use a water-resistant product if swimming or sweating. Reapply at least every 2 hours. Children under 6 months: Ask a doctor. Sun Protection Measures: Spending time in the sun increases your risk of skin cancer and early skin aging. To decrease this risk, regularly use a sunscreen with a Broad-Spectrum SPF value of 15 or higher and other sun protection measures including: Limit time in the sun, especially from 10 a.m. - 2 p.m. Wear long-sleeved shirts, pants, hats and sunglasses.

Inactive Ingredients:

Alumina, Aluminum Hydroxide, Aluminum Stearate, Asorbic Acid, Ascorbyl Palmitate, C12-15Alkyl Benzoate, Cetearyl Isononanoate, Cetyl PEG/PPG-15/15 Butyl Ether Dimethicone, Citric Acid, Dipropylene Glycol Dicaprylate-Caprate, Ethylhexyl Palmitate, Flavor, Helianthus annuus (Sunflower) Seed Wax, Hexyldecanol, Hexyldecyl Laurate, Iron Oxide, Lecithin, Ozokerite, PEG-8, Polyglyceryl-3 Diisostearate, Polyhydroxystearic Acid, Stearic Acid, Tocopherol, Tocopheryl Acetate, Zingiber Officinale (Ginger) Root Oil

Other Information:

reef friendly

cruelty free

non-comedogenic